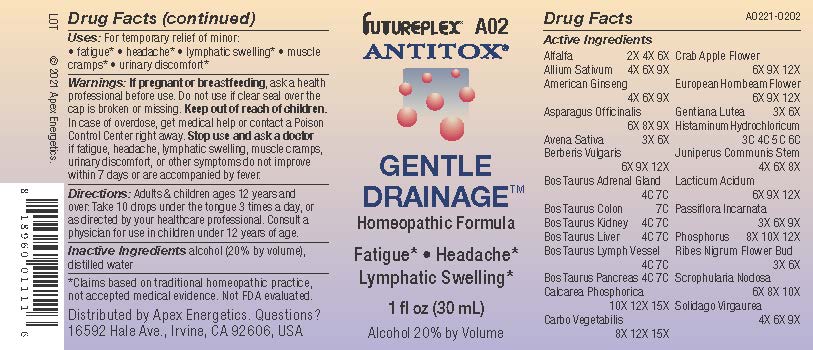 DRUG LABEL: A02
NDC: 63479-0102 | Form: SOLUTION/ DROPS
Manufacturer: Apex Energetics Inc.
Category: homeopathic | Type: HUMAN OTC DRUG LABEL
Date: 20240108

ACTIVE INGREDIENTS: ACTIVATED CHARCOAL 15 [hp_X]/1 mL; GENTIANA LUTEA ROOT 6 [hp_X]/1 mL; SCROPHULARIA NODOSA 10 [hp_X]/1 mL; SOLIDAGO VIRGAUREA FLOWERING TOP 9 [hp_X]/1 mL; ALFALFA 6 [hp_X]/1 mL; MALUS SYLVESTRIS FLOWER 12 [hp_X]/1 mL; BOS TAURUS ADRENAL GLAND 7 [hp_C]/1 mL; CARPINUS BETULUS FLOWER 12 [hp_X]/1 mL; AVENA SATIVA FLOWERING TOP 6 [hp_X]/1 mL; BEEF KIDNEY 7 [hp_C]/1 mL; LACTIC ACID, DL- 12 [hp_X]/1 mL; PHOSPHORUS 12 [hp_X]/1 mL; RIBES NIGRUM FLOWER BUD 6 [hp_X]/1 mL; ASPARAGUS 9 [hp_X]/1 mL; GARLIC 9 [hp_X]/1 mL; AMERICAN GINSENG 9 [hp_X]/1 mL; HISTAMINE DIHYDROCHLORIDE 6 [hp_C]/1 mL; JUNIPERUS COMMUNIS STEM 8 [hp_X]/1 mL; PASSIFLORA INCARNATA FLOWERING TOP 9 [hp_X]/1 mL; BERBERIS VULGARIS ROOT BARK 12 [hp_X]/1 mL; BOS TAURUS COLON 7 [hp_C]/1 mL; BEEF LIVER 7 [hp_C]/1 mL; BOS TAURUS LYMPH VESSEL 7 [hp_C]/1 mL; BOS TAURUS PANCREAS 7 [hp_C]/1 mL; TRIBASIC CALCIUM PHOSPHATE 15 [hp_X]/1 mL
INACTIVE INGREDIENTS: WATER; ALCOHOL

A02

Active Ingredients
Alfalfa | 2X 4X 6X
Allium Sativum | 4X 6X 9X
American Ginseng | 4X 6X 9X
Asparagus Officinalis | 6X 8X 9X
Avena Sativa | 3X 6X
Berberis Vulgaris | 6X 9X 12X
Bos Taurus Adrenal Gland | 4C 7C
Bos Taurus Colon | 7C
Bos Taurus Kidney | 4C 7C
Bos Taurus Liver | 4C 7C
Bos Taurus Lymph Vessel | 4C 7C
Bos Taurus Pancreas | 4C 7C
Calcarea Phosphorica | 10X 12X 15X
Carbo Vegetabilis | 8X 12X 15X
Crab Apple Flower | 6X 9X 12X
European Hornbeam Flower | 6X 9X 12X
Gentiana Lutea | 3X 6X
Histaminum Hydrochloricum | 3C 4C 5C 6C
Juniperus Communis Stem | 4X 6X 8X
Lacticum Acidum | 6X 9X 12X
Passiflora Incarnata | 3X 6X 9X
Phosphorus | 8X 10X 12X
Ribes Nigrum Flower Bud | 3X 6X
Scrophularia Nodosa | 6X 8X 10X
Solidago Virgaurea | 4X 6X 9X

INDICATIONS AND USAGE

Uses:

For temporary relief of minor:

fatigue*

headache*

lymphatic swelling*

muscle cramps*

urinary discomfort*

*Claims based on traditional homeopathic practice, not accepted medical evidence. Not FDA evaluated.

Warnings:

PREGNANCY OR BREAST FEEDING

If pregnant or breastfeeding, ask a health professional before use.

Do not use if clear seal over the cap is broken or missing.

Keep out of reach of children. In case of overdose, get medical help or contact a Poison Control Center right away.

Stop use and ask a doctor if fatigue, headache, lymphatic swelling, muscle cramps, urinary discomfort, or other symptoms do not improve within 7 days or are accompanied by fever.

Directions:

Adults & children ages 12 years and over: Take 10 drops under the tongue 3 times a day, or as directed by your healthcare professional. Consult a physician for use in children under 12 years of age.

Inactive Ingredients

alcohol (20% by volume), distilled water

Distributed by Apex Energetics. Questions?

16592 Hale Ave., Irvine, CA 92606, USA

PACKAGE LABEL

FUTUREPLEX® A02

ANTITOX®

GENTLE DRAINAGE™

Homeopathic Formula

Fatigue*

Headache*

Lymphatic Swelling*

1 fl oz (30 mL)

Alcohol 20% by Volume